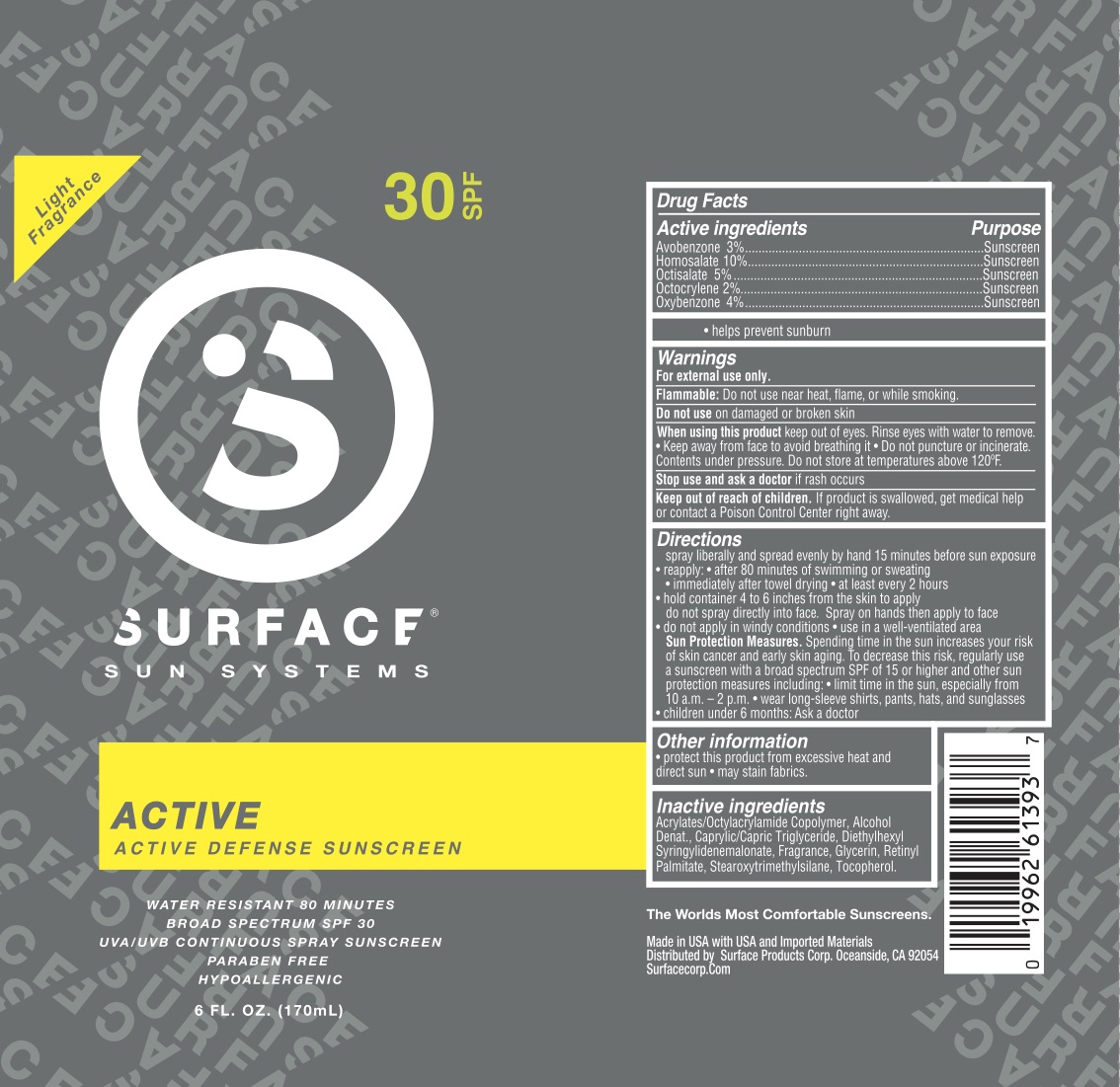 DRUG LABEL: Surface Sun Active Defense SPF 30 Sunscreen
NDC: 72344-010 | Form: SPRAY
Manufacturer: Surface Products Corp
Category: otc | Type: HUMAN OTC DRUG LABEL
Date: 20180531

ACTIVE INGREDIENTS: AVOBENZONE 3 g/100 mL; HOMOSALATE 10 g/100 mL; OCTISALATE 5 g/100 mL; OXYBENZONE 4 g/100 mL; OCTOCRYLENE 2 g/100 mL
INACTIVE INGREDIENTS: TOCOPHEROL; VITAMIN A PALMITATE; ALCOHOL; GLYCERIN; MEDIUM-CHAIN TRIGLYCERIDES; DIETHYLHEXYL SYRINGYLIDENEMALONATE; ACRYLATE/ISOBUTYL METHACRYLATE/N-TERT-OCTYLACRYLAMIDE COPOLYMER (75000 MW); STEAROXYTRIMETHYLSILANE

Active Ingredients

Avobenzone 3%, Homosalate 10%, Octisalate 5%, Octocrylene 2%, Oxybenzone 4%

Purpose

Sunscreen

Use

Helps prevent sunburn.

Warnings

For external use only.

Flammable: do not use near heat, flame, or while smoking. Do not use on damaged or broken skin. When using this product keep out of eyes. Rinse eyes with water to remove. Keep away from face to avoid breathing it. Do not puncture or incinerate. Contents under pressure. Do not store at temperatures above 120F. Stop use and ask a doctor if rash occurs.

Keep Out of Reach of Children.

If product is swallowed, get medical help or contact a Poison Control Center right away.

Directions

Spray liberally and evenly by hand 15 minutes before sun exposure.

Reapply after:

80 minutes of sweating or swimming
immediately after towel drying
at least every 2 hours

Hold can 4-6 inches from the skin to apply. Do not spray directly into your face. Spray on hands an then apply to face. Do not apply in windy conditions. Use in a well-ventilated area.

Sun Protection Measures: Spending time in the sun increases your risk of skin cancer and early skin aging. To decrease this risk, regularly use a sunscreen with a broad spectrum SPF of 15 or higher and other sun protection measures including:
Limit time in the sun, especially from 10 a.m. - 2 p.m.
Wear long-sleeved shirts, pants, hats, and sunglasses.

Children under 6 months: ask a doctor.

Inactive Ingredients

Acrylates/Octylacrylamide Crosspolymer, Alcohol Denat., Caprylic/Capric Triglyceride, Diethylhexyl Syringylidenemalonate, Fragrance, Glycerin, Retinyl Palmitate, Stearoxytrimethylsilane, Tocopherol.